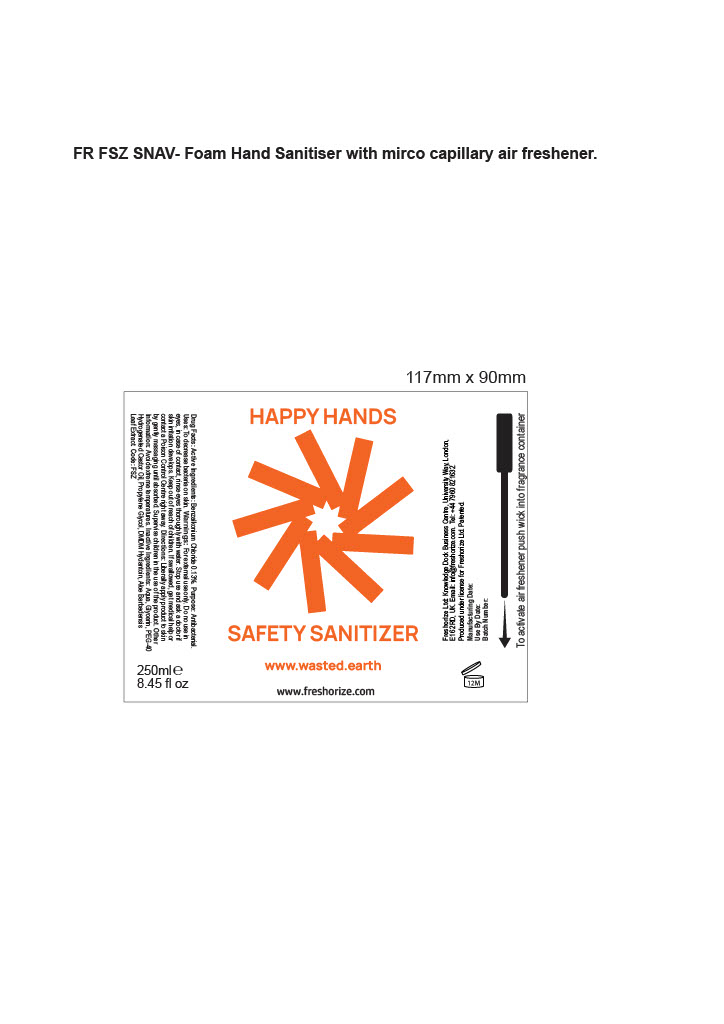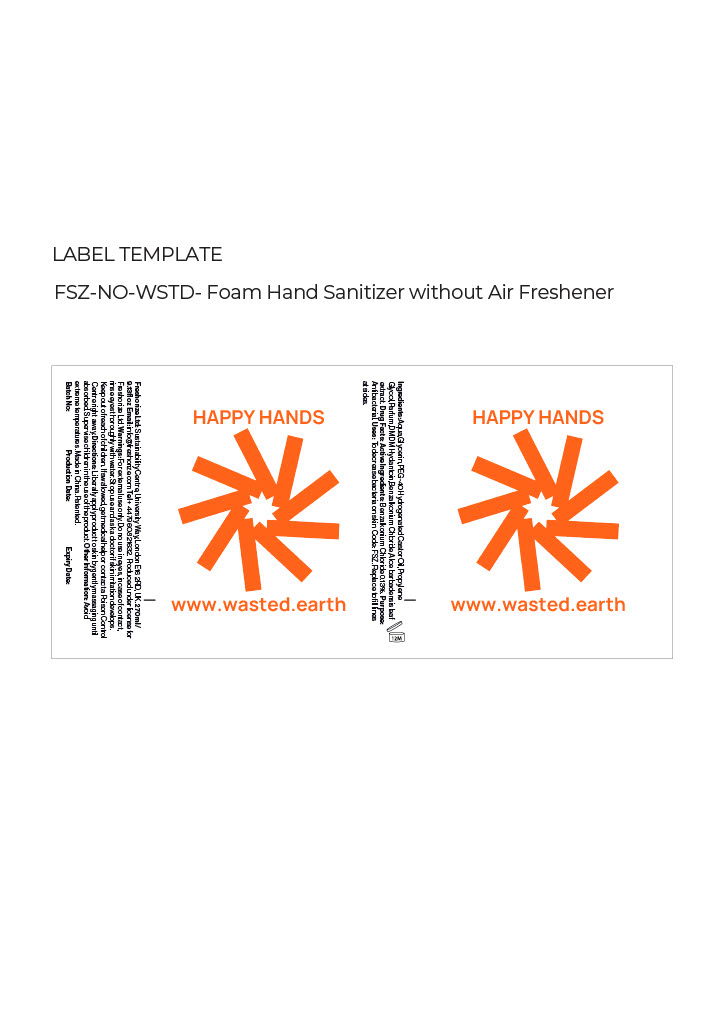 DRUG LABEL: Wasted
NDC: 52305-802 | Form: LIQUID
Manufacturer: Freshorize Ltd
Category: otc | Type: HUMAN OTC DRUG LABEL
Date: 20251023

ACTIVE INGREDIENTS: BENZALKONIUM CHLORIDE 0.13 g/100 mL; HYDROGENATED CASTOR OIL 0.75 g/100 mL
INACTIVE INGREDIENTS: ALOE VERA LEAF 0.1 g/100 mL; GLYCERIN 5 g/100 mL; PROPYLENE 0.5 g/100 mL; WATER 93.07 g/100 mL; DMDM HYDANTOIN 0.2 g/100 mL

Wasted Happy Hands Safety Sanitizer

Warnings:

Warnings: For external use only. Do no use in eyes, in case of contact, rinse eyes thoroughly with water.

Stop use and ask a doctor if contact a skin irritation develops. Keep out of children. If swallowed,get medical help or contact a Poison Control Centre right away

Warnings:

Keep out of reach of children.

Directions:

Directions: Liberally apply product to skin by gently massaging until absorbed. Supervise children in the use of the product.

Uses:

Uses: To decrease bacteria on skin.

Purpose:

Purpose: Antibacterial.

Drug facts:

Drug Facts: Active Ingredients: Benzalkonium Chloride 0.13%.

Inactive Ingredients:

Inactive Ingredients: Aqua, Glycerin, PEG-40, Hydrogenated Castor Oil, Propylene Glycol, DMDM Hydantoin, Aloe Barbadensis Leaf Extract.

Other Information:

Other Information: Avoid extreme temperatures.

Happy Hands Safety Sanitizer

Happy Hands Sanitizer

This is a pump item with no dosage information. Most customers use 1-2 pumps.